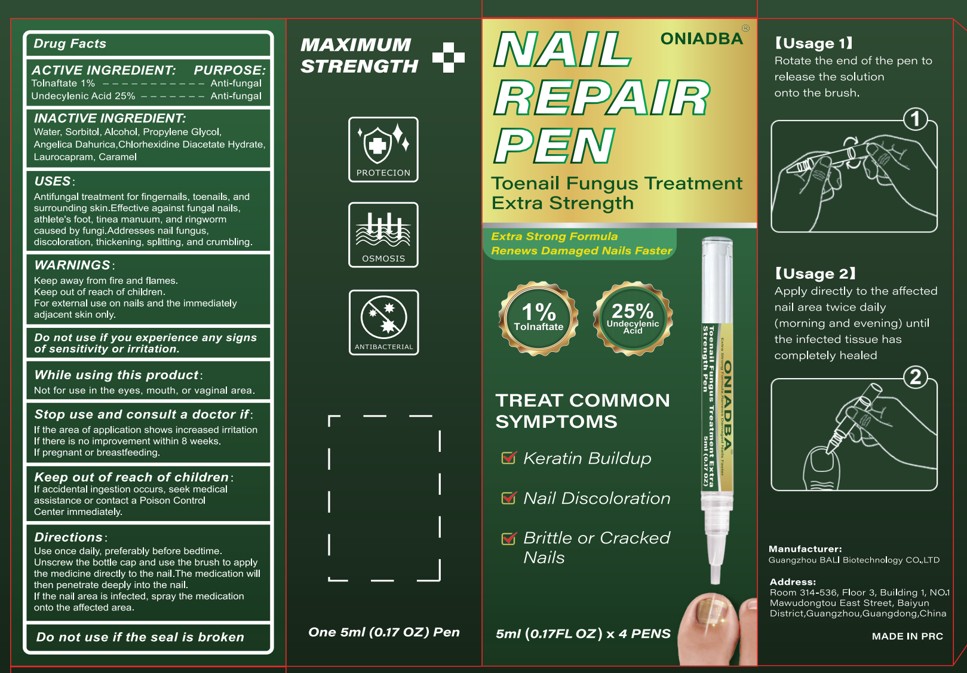 DRUG LABEL: ONIADBA Nail Fungus Treatment Pen
NDC: 85992-004 | Form: LIQUID
Manufacturer: Shenzhen Boyimei Technology Co., Ltd.
Category: otc | Type: HUMAN OTC DRUG LABEL
Date: 20250806

ACTIVE INGREDIENTS: TOLNAFTATE 1 g/100 mL; UNDECYLENIC ACID 25 g/100 mL
INACTIVE INGREDIENTS: LAUROCAPRAM; CHLORHEXIDINE DIACETATE; ALCOHOL; CARAMEL; WATER; SORBITOL; PROPYLENE GLYCOL; ANGELICA DAHURICA ROOT

85992-004 ONIADBA Nail Fungus Treatment Pen

ACTIVE INGREDIENT

Tolnaftate 1%
Undecylenic Acid 25%

PURPOSE

Anti-fungal

INDICATIONS AND USAGE

Antifungal treatment for fingernails, toenails, and surrounding skin.Effective against fungal nails.athlete's foot, tinea manuum, and ringworm caused by fungi.Addresses nail fungus,discoloration, thickening, splitting, and crumbling

WARNINGS

Keep away from fire and flames.
Keep out of reach of children.
For external use on nails and the immediately adjacent skin only.

Do not use if you experience any signsof sensitivity or irritation.

WHEN USING

Not for use in the eyes, mouth, or vaginal area

STOP USE

If the area of application shows increased irritation
If there is no improvement within 8 weeks.
If pregnant or breastfeeding.

KEEP OUT OF REACH OF CHILDREN

If accidental ingestion occurs, seek medical
assistance or contact a Poison Control
Center immediately.

DOSAGE AND ADMINISTRATION

Water, Sorbitol, Alcohol, Propylene Glycol,Angelica Dahurica,Chlorhexidine Diacetate Hydrate, Laurocapram, Caramel

INACTIVE INGREDIENT

Water, Sorbitol, Alcohol, Propylene Glycol,Angelica Dahurica,Chlorhexidine Diacetate Hydrate, Laurocapram, Caramel